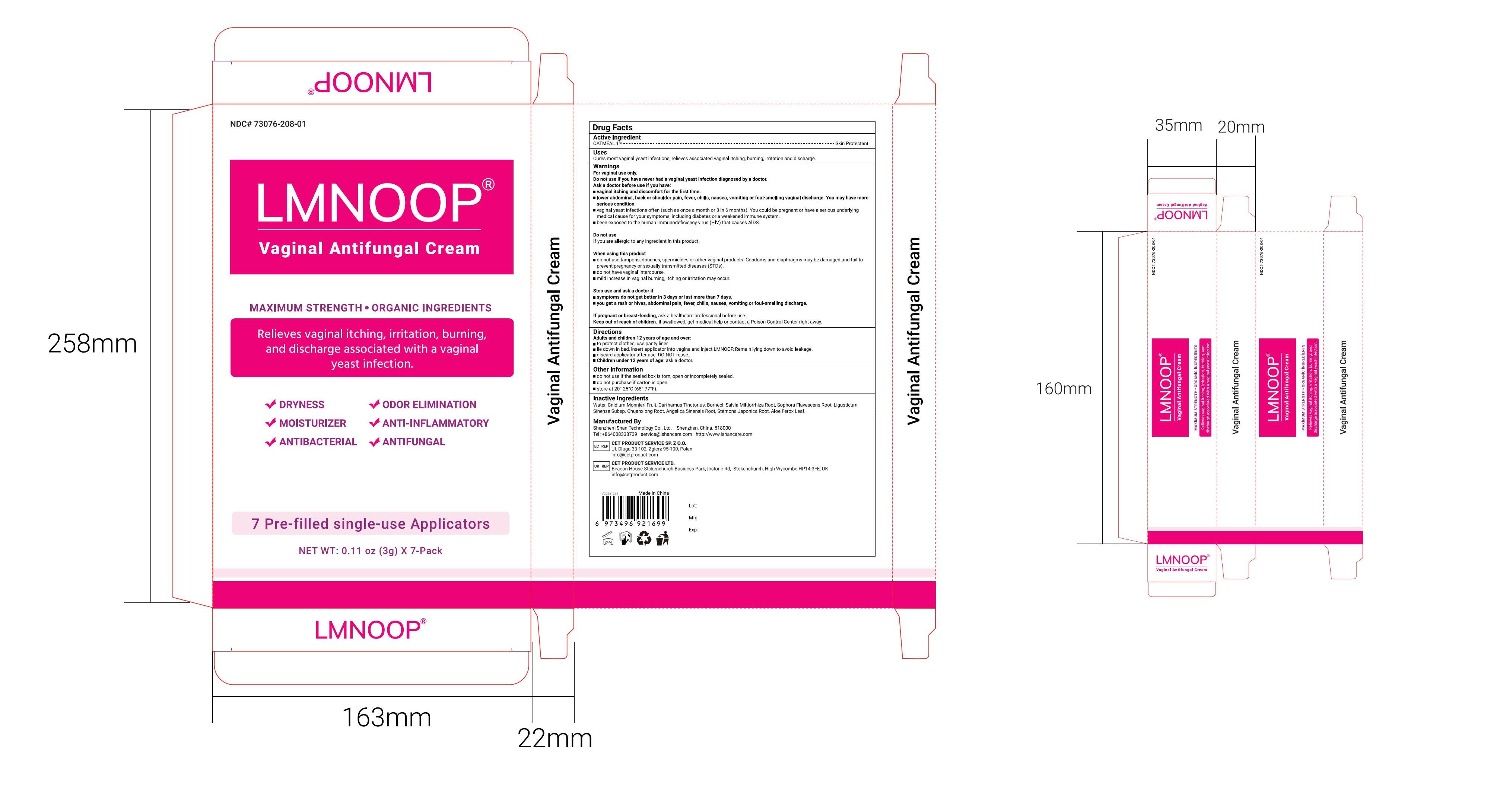 DRUG LABEL: LMNOOP Vaginal Antifungal Cream
NDC: 73076-208 | Form: CREAM
Manufacturer: Shenzhen Ishan Technology Co., Ltd
Category: homeopathic | Type: HUMAN OTC DRUG LABEL
Date: 20260212

ACTIVE INGREDIENTS: OATMEAL 1 g/100 g
INACTIVE INGREDIENTS: SALVIA MILTIORRHIZA ROOT 1.5 g/100 g; ANGELICA SINENSIS ROOT 0.5 g/100 g; CNIDIUM MONNIERI FRUIT 2 g/100 g; STEMONA JAPONICA ROOT 0.5 g/100 g; ALOE FEROX LEAF 0.5 g/100 g; LIGUSTICUM SINENSE SUBSP. CHUANXIONG ROOT 1 g/100 g; CARTHAMUS TINCTORIUS (SAFFLOWER) OLEOSOMES 2 g/100 g; SOPHORA FLAVESCENS ROOT 1.5 g/100 g; WATER 87.5 g/100 g

Active ingredients

Oatmeal--1%--Skin protectant.

Inactive Ingredients

Purify water, dictamnus dasycarpus root, stellera chamaejasme whole, sophora flavescens root, cnidium monnieri fruit, phellodendron chinense whole, bassia scoparia fruit, Menthol.

Keep out of reach of children

if swallowed, call poison control or seek medical help.

Ask a doctor

if you have never had a vaginal yeast infection diagnosed by a doctor.
Ask a doctor before use if you have:
* vaginal itching and discomfort for the first time.

* lower abdominal, back or shoulder pain, fever, chills, nausea, vomiting or fou-smeling vaginal discharge. You may have moreserious condition.
* vaginal yeast infections often (such as once a month or 3 in 6 months). You could be pregnant or have a serious underlyingmedical cause for your symptoms, including diabetes or a weakened immune system.

* been exposed to the human immunodeficiency virus (HiV) that causes AlDS.

Stop use

* symptoms do not get better in 3 days or last more than 7 days.
* you get a rash or hives, abdominal pain, fever, chills, nausea, vomiting or foul-smelling discharge.

Uses

Cures most vaginal yeast infections, relieves associated vaginal itching, burning, irritation and discharge.

Other information

do not use if the sealed box is torn, open or incompletely sealed
do not purchase if carton is open.
store at 20°-25°C(68°-77°F).

Directions

Adults and children 12 years of age and over:

* to protect clothes, use panty liner.
* lie down in bed, insert applicator into vagina and inject LMNOOP, Remain lying down to avoid leakage.
* discard applicator after use. DO NOT reuse.
* Children under 12 years of age: ask a doctor.

When using this product

* do not use tampons, douches, spermicides or other vaginal products. Condoms and diaphragms may be damaged and fail toprevent pregnancy or sexually transmitted diseases (STDs).

* do not have vaginal intercourse.
* mild increase in vaginal burning, itching or irritation may occur.

Warnings

For vaginal use only.